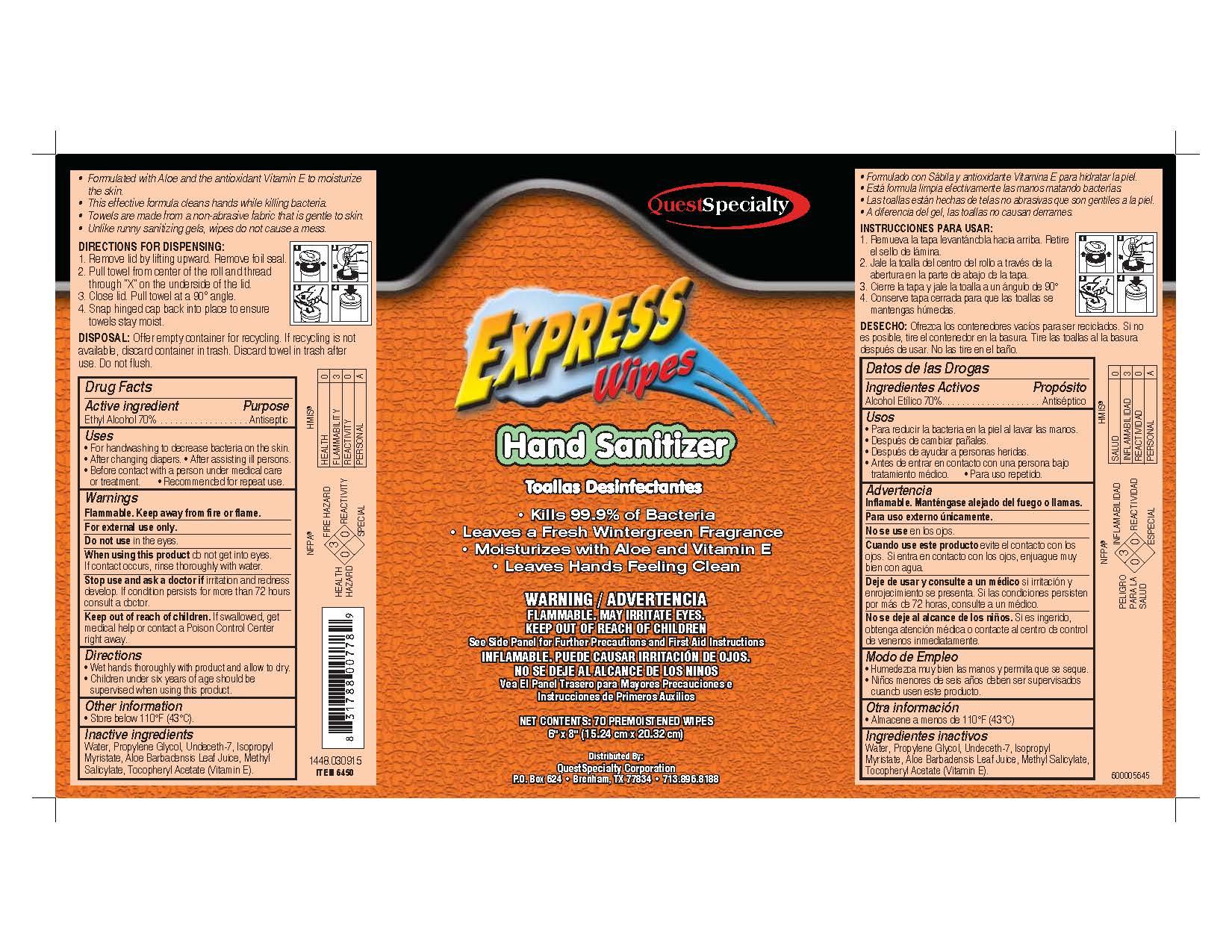 DRUG LABEL: Express Wipes Hand Sanitizer
NDC: 67858-645 | Form: LIQUID
Manufacturer: QuestSpecialty Corporation
Category: otc | Type: HUMAN OTC DRUG LABEL
Date: 20241206

ACTIVE INGREDIENTS: ALCOHOL 7 g/10 g
INACTIVE INGREDIENTS: WATER

Hand Sanitizer Wipe QS

label

Active Ingredient Purpose

Ethyl Alcohol 70%...... Antiseptic

Stop use and ask a doctor if irritation and redness develop. If condition persists for more than 72 hours consulta a doctor.

Do not use in the eyes.

WARNINGS

Flammable. Keep awaay from fire or flame.

For external use only.

KEEP OUT OF REACH OF CHILDREN

Keep out of reah of children. If swallowed, get medical help or contact a Poison Cotnrol Center righ away.

STORAGE AND HANDLING

- Store below 110oF (43oC).

INACTIVE INGREDIENT

Water, Propylene Glycol, Undeceth-7, Isopropyl Myristate, Aloe Barbacdensis Leaf Juice, Methyl Salicylae, Tocophenyl Aceate (Vitamin E).

INDICATIONS AND USAGE

- For handwashing to decrease bacterial on the skin.
- After changing diapers.
- After assisting ill persons.
- Before contact with a person under medical care or treatment.
- Recommended for repeat use.

DOSAGE AND ADMINISTRATION

- Wet hands thoroughly with product and allow to dry.,
- Children under six years of age shoudl be supervised when using this product.

PURPOSE

Antiseptic